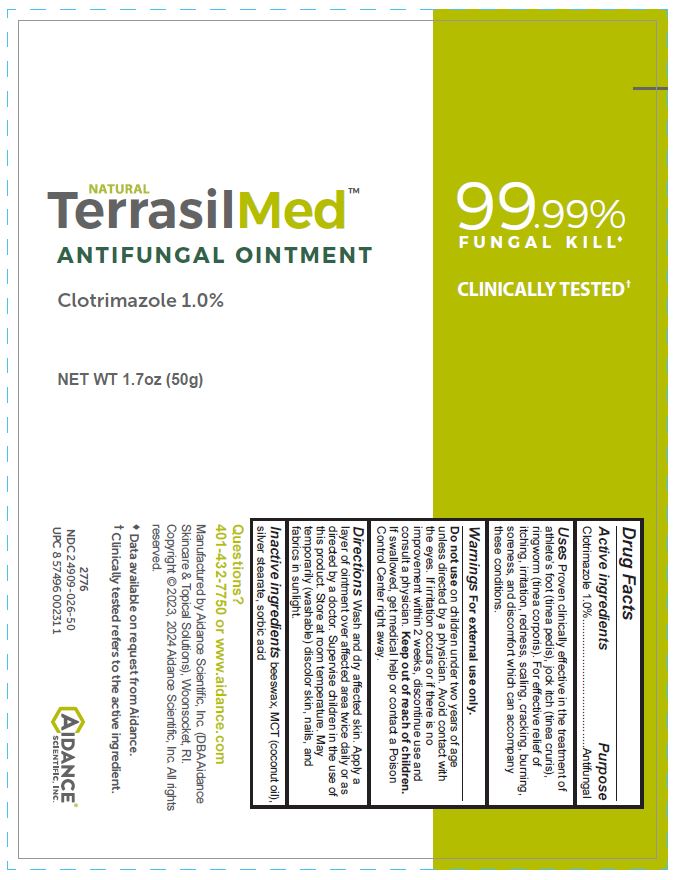 DRUG LABEL: TerrasilMed ANTIFUNGAL
NDC: 24909-026 | Form: OINTMENT
Manufacturer: Aidance Scientific, Inc., DBA Aidance Skincare & Topical Solutions
Category: otc | Type: HUMAN OTC DRUG LABEL
Date: 20241125

ACTIVE INGREDIENTS: CLOTRIMAZOLE 1 g/100 g
INACTIVE INGREDIENTS: YELLOW WAX; COCONUT OIL; SILVER STEARATE; SORBIC ACID

24909-026 TerrasilMed ANTIFUNGAL

Active ingredient

Clotrimazole 1.0%

Pupose

Antifungal

Uses

Proven clinically effective in the treatment of athlete’s foot (tinea pedis), jock itch (tinea cruris), ringworm (tinea corporis). For effective relief of itching, irritation, redness, scaling, cracking, burning, soreness, and discomfort which can accompany these conditions.

Warnings

For external use only.

Do not use on children under two years of age unless directed by a physician. Avoid contact with the eyes. If irritation occurs or if there is no improvement within 2 weeks, discontinue use and consult a physician.

Keep out of reach of children.

OTHER SAFETY INFORMATION

If swallowed, get medical help or contact a Poison Control Center right away.

Directions

Wash and dry affected skin. Apply a layer of ointment over affected area twice daily or as directed by a doctor. Supervise children in the use of this product. Store at room temperature. May temporarily (washable) discolor skin, nails, and fabrics in sunlight.

Inactive ingredients

beeswax, MCT (coconut oil), silver stearate, sorbic acid

Questions?

401-432-7750 or www.aidance.com